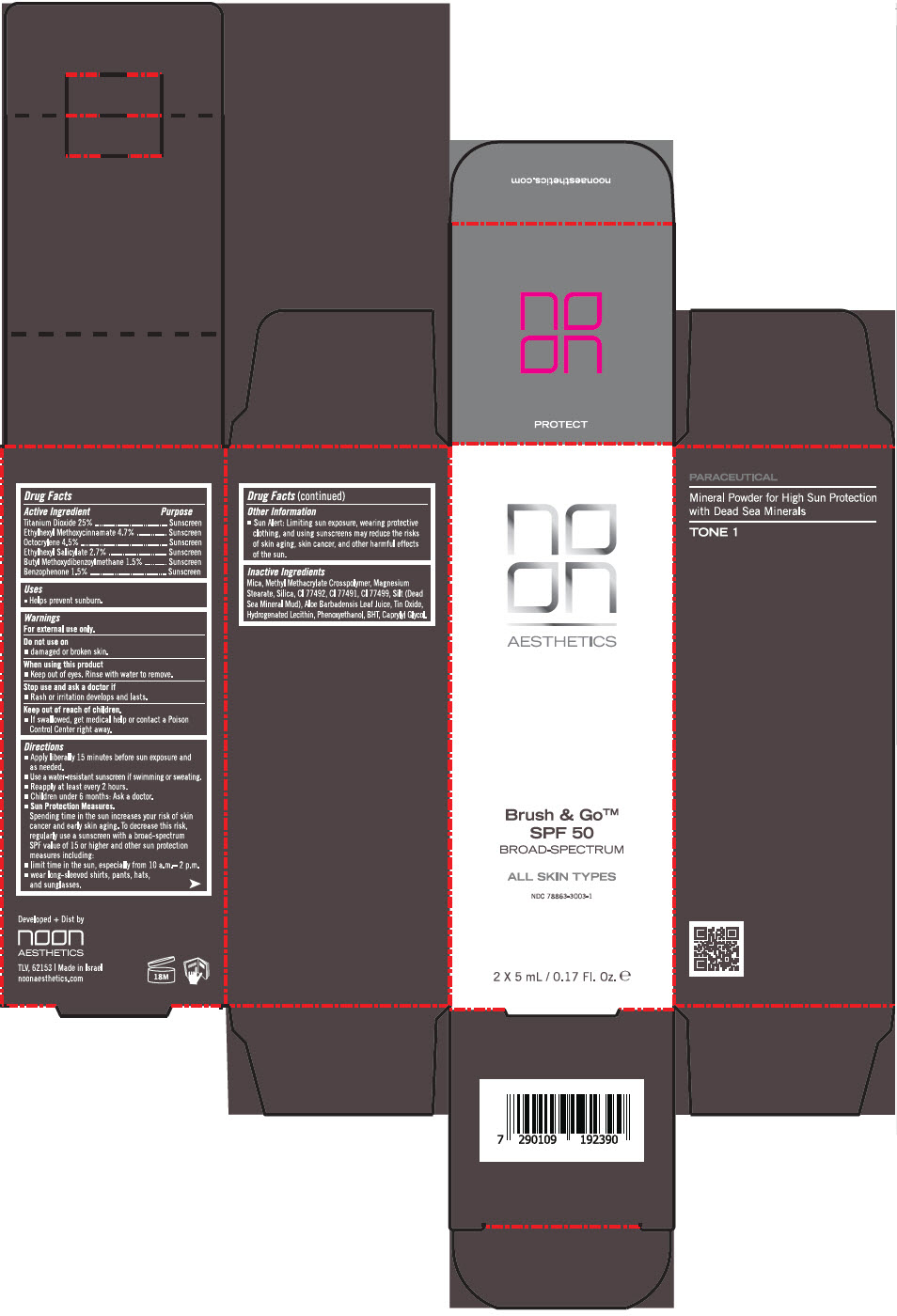 DRUG LABEL: BRUSH and GO SPF 50 
NDC: 78863-3003 | Form: POWDER
Manufacturer: Noon Aesthetics M.R. Ltd
Category: otc | Type: HUMAN OTC DRUG LABEL
Date: 20260116

ACTIVE INGREDIENTS: TITANIUM DIOXIDE 0.75 g/5 mL; OCTINOXATE 0.141 g/5 mL; OCTOCRYLENE 0.135 g/5 mL; OCTISALATE 0.08 g/5 mL; AVOBENZONE 0.045 g/5 mL; OXYBENZONE 0.045 g/5 mL
INACTIVE INGREDIENTS: MICA; METHYL METHACRYLATE/GLYCOL DIMETHACRYLATE CROSSPOLYMER; MAGNESIUM STEARATE; SILICON DIOXIDE; FERRIC OXIDE YELLOW; FERRIC OXIDE RED; FERROSOFERRIC OXIDE; ALOE VERA LEAF; STANNOUS OXIDE; PHENOXYETHANOL; BUTYLATED HYDROXYTOLUENE; CAPRYLYL GLYCOL

BRUSH & GO™ SPF 50
ALL SKIN TYPES BROAD SPECTRUM

DRUG FACTS INFORMATION

ACTIVE INGREDIENT

Active Ingredients / Purpose:
Titanium Dioxide 25% | Sunscreen
Ethylhexyl Methoxycinnamate 4.7% | Sunscreen
Octocrylene 4.5% | Sunscreen
Ethylhexyl Salicylate 2.7% | Sunscreen
Butyl Methoxydibenzoylmethane 1.5% | Sunscreen
Benzophenone 1.5% | Sunscreen

Uses

Helps prevent sunburn.

Warnings

For external use only.

Do not use

- On damaged or broken skin.

When using this product

- Keep out of eyes. Rinse with water to remove.

Stop use and ask a doctor if

- Rash or irritation develops and lasts.

Keep out of reach of children.

- If swallowed, get medical help or contact a Poison Control Center right away.

Directions

- Apply liberally 15 minutes before sun exposure and as needed.
- Use a water-resistant sunscreen if swimming or sweating.
- Reapply at least every 2 hours.
- Children under 6 months: Ask a doctor.
- Sun Protection Measures.
  Spending time in the sun increases your risk of skin cancer and early skin aging. To decrease this risk, regularly use a sunscreen with a broad-spectrum SPF value of 15 or higher and other sun protection measures including:
  - limit time in the sun, especially from 10 a.m.– 2 p.m.
  - wear long-sleeved shirts, pants, hats, and sunglasses.

Other Information

- Sun alert: Limiting sun exposure, wearing protective clothing, and using sunscreens may reduce the risks of skin aging, skin cancer, and other harmful effects of the sun.

Questions or comments?

Visit www.noonaesthetics.com or call toll free1-833-666-6246

Inactive Ingredients

Mica, Methyl Methacrylate Crosspolymer, Magnesium Stearate, Silica, CI 77492, CI 77491, CI 77499, Silt (Dead Sea Mineral Mud), Aloe Barbadensis Leaf Juice, Tin Oxide, Hydrogenated Lecithin, Phenoxyethanol, BHT, Caprylyl Glycol

Developed + Dist by
noon AESTHETICS
TLV, 62153

PRINCIPAL DISPLAY PANEL - 5 mL Bottle Carton

no
on
AESTHETICS

Brush & Go™
SPF 50

BROAD-SPECTRUM

ALL SKIN TYPES

NDC 78863-3003-1

2 X 5 mL / 0.17 Fl. Oz. ℮